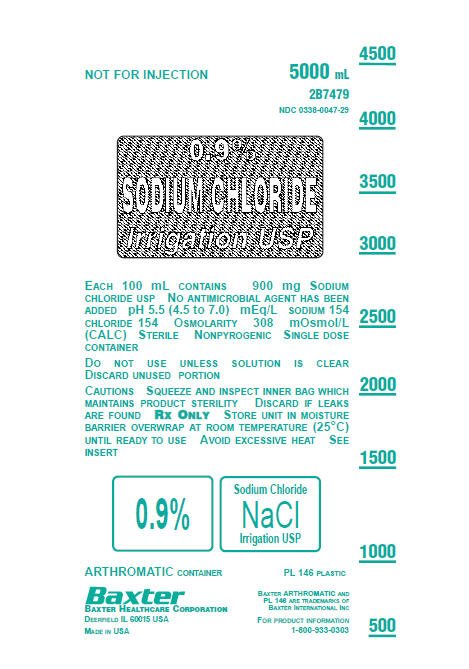 DRUG LABEL: Sodium Chloride
NDC: 0338-0047 | Form: IRRIGANT
Manufacturer: Baxter Healthcare Corporation
Category: prescription | Type: HUMAN PRESCRIPTION DRUG LABEL
Date: 20180717

ACTIVE INGREDIENTS: SODIUM CHLORIDE 900 mg/100 mL
INACTIVE INGREDIENTS: WATER

0.9% Sodium Chloride Irrigation, USP
in ARTHROMATIC Plastic Container

DESCRIPTION

0.9% Sodium Chloride Irrigation, USP is a sterile nonpyrogenic, isotonic solution in a single dose ARTHROMATIC plastic container for use as an arthroscopic irrigating solution. Each liter contains 9 g Sodium Chloride, USP (NaCl) in Water for Injection. pH 5.5 (4.5 to 7.0). Milliequivalents per liter: Sodium - 154, Chloride - 154. Osmolarity 308 mOsmol/L (calc.). No antimicrobial agent has been added.

The ARTHROMATIC plastic container is fabricated from a specially formulated polyvinyl chloride (PL 146 Plastic). The amount of water that can permeate from inside the container into the overwrap is insufficient to affect the solution significantly. Solutions in contact with the plastic container can leach out certain of its chemical components in very small amounts within the expiration period, e.g., di-2-ethylhexylphthalate (DEHP), up to 5 parts per million. However, the safety of the plastic has been confirmed in tests in animals according to USP biological tests for plastic containers as well as by tissue culture toxicity studies.

CLINICAL PHARMACOLOGY

0.9% Sodium Chloride Irrigation, USP is useful as an irrigating fluid for body joints because the solution is isotonic, and provides a transparent fluid medium with optical properties suitable for good visualization of the interior joint surface during endoscopic examination. During arthroscopic surgical procedures, the solution acts as a lavage for removing blood, tissue fragments, and bone fragments.

INDICATIONS AND USAGE

0.9% Sodium Chloride Irrigation, USP is indicated for use as an arthroscopic irrigating fluid with endoscopic instruments during arthroscopic procedures requiring distension and irrigation of the knee, shoulder, elbow, or other bone joints.

CONTRAINDICATIONS

None known.

WARNINGS

Not for injection.

Because fluids used to irrigate joints may be absorbed into the general circulation, solutions containing sodium ion should be used with great care in patients with congestive heart failure, severe renal insufficiency, and in clinical states in which there exists edema with sodium retention.

The contents of an opened container should be used promptly to minimize the possibility of bacterial growth or pyrogen formation. Discard the unused portion of irrigating solution since no antimicrobial agent has been added.

PRECAUTIONS

Because some of the fluid used to irrigate joints may be absorbed, caution must be exercised in the volume of irrigating fluid used especially with solutions containing the sodium ion in patients receiving corticosteroids or corticotropin.

Pediatric Use

Safety and effectiveness in pediatric patients have not been established.

Do not administer unless the solution is clear and the seal is intact.

ADVERSE REACTIONS

None known.

DOSAGE AND ADMINISTRATION

The volume of solution needed will vary with the nature and duration of the arthroscopic procedure.

If desired, warm in overpouch to near body temperature in a water bath or oven heated to not more than 45º C.

Parenteral drug products should be inspected visually for particulate matter and discoloration prior to administration whenever solution and container permit.

HOW SUPPLIED

0.9% Sodium Chloride Irrigation, USP in ARTHROMATIC Plastic Container is available as follows:

2B7477 | 3000 mL | NDC 0338-0047-27
2B7479 | 5000 mL | NDC 0338-0047-29

Exposure of pharmaceutical products to heat should be minimized. Avoid excessive heat. It is recommended the product be stored at room temperature (25º C); brief exposure up to 40º C does not adversely affect the product.

DIRECTIONS FOR USE

Tear overwrap down side at slit and remove solution container. Visually inspect the container. If the outlet port protector is damaged, detached, or not present, discard container as solution path sterility may be impaired. Some opacity of the plastic due to moisture absorption during the sterilization process may be observed. This is normal and does not affect the solution quality or safety. The opacity will diminish gradually. Check for minute leaks by squeezing bag firmly. If leaks are found, discard solution as sterility may be impaired.

Use Aseptic Technique.

1. Suspend container using hanger hole.
2. Remove protector from outlet port.
3. Attach irrigation set. Refer to complete directions accompanying set.

Baxter Healthcare Corporation

Deerfield, IL 60015 USA

Printed in USA

07-19-00-0407
Rev. July 2018

Baxter and Arthromatic are trademarks of Baxter International Inc.

PACKAGE LABEL.PRINCIPLE DISPLAY PANEL

0.9% Sodium Chloride Irrigation USP Container Label

0.9% Sodium Chloride Irrigation USP Container Label

NOT FOR INJECTION

5000 mL

2B7479

NDC 0338-0047-29

0.9% SODIUM CHLORIDE Irrigation USP

EACH 100 mL CONTAINS 900 mg SODIUM

CHLORIDE USP NO ANTIMICROBIAL AGENT HAS BEEN

ADDED pH 5.5 (4.5 to 7.0) mEq/L SODIUM 154

CHLORIDE 154 OSMOLARITY 308 mOsmol/L

(CALC) STERILE NONPYROGENIC SINGLE DOSE

CONTAINER

DO NOT USE UNLESS SOLUTION IS CLEAR

DISCARD UNUSED PORTION

CAUTIONS SQUEEZE AND INSPECT INNER BAG WHICH

MAINTAINS PRODUCT STERILITY DISCARD IF LEAKS

ARE FOUND RX ONLY STORE UNIT IN MOISTURE

BARRIER OVERWRAP AT ROOM TEMPERATURE (25°C)

UNTIL READY TO USE AVOID EXCESSIVE HEAT SEE

INSERT

0.9% Sodium Chloride NaCl Irrigation USP

ARTHROMATIC CONTAINER PL 146 PLASTIC

BAXTER HEALTHCARE CORPORATION

DEERFIELD IL 60015 USA

MADE IN USA

BAXTER ARTHROMATIC AND

PL 146 ARE TRADEMARKS OF

BAXTER INTERNATIONAL INC

FOR PRODUCT INFORMATION

1-800-933-0303